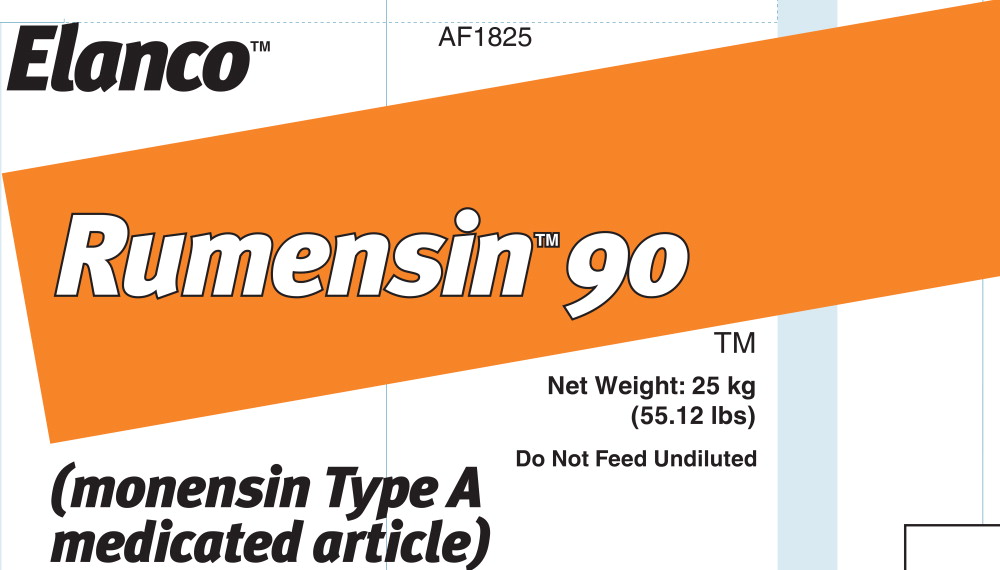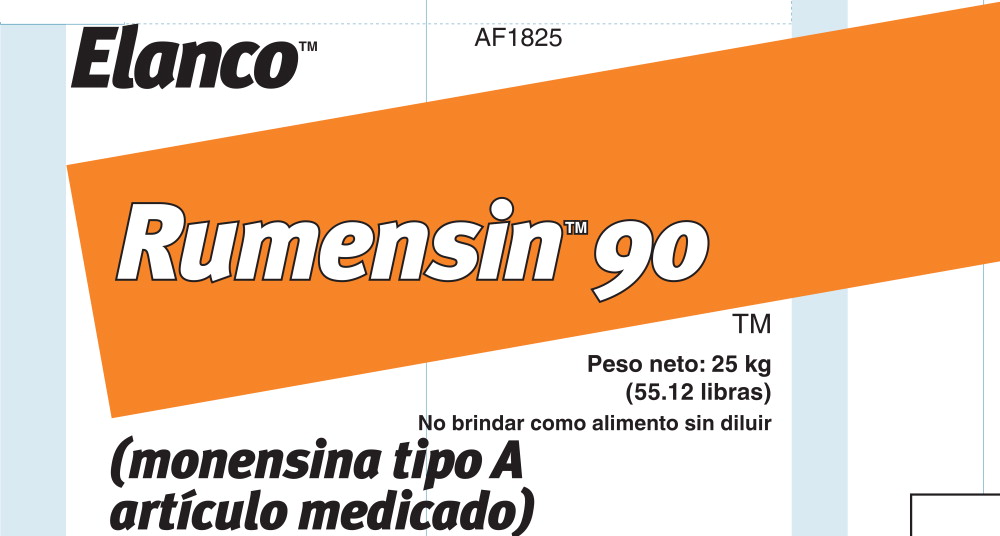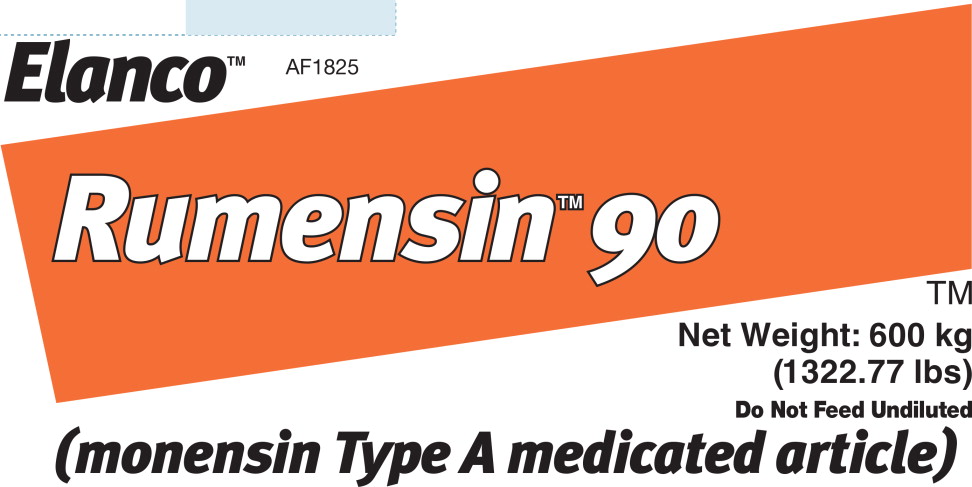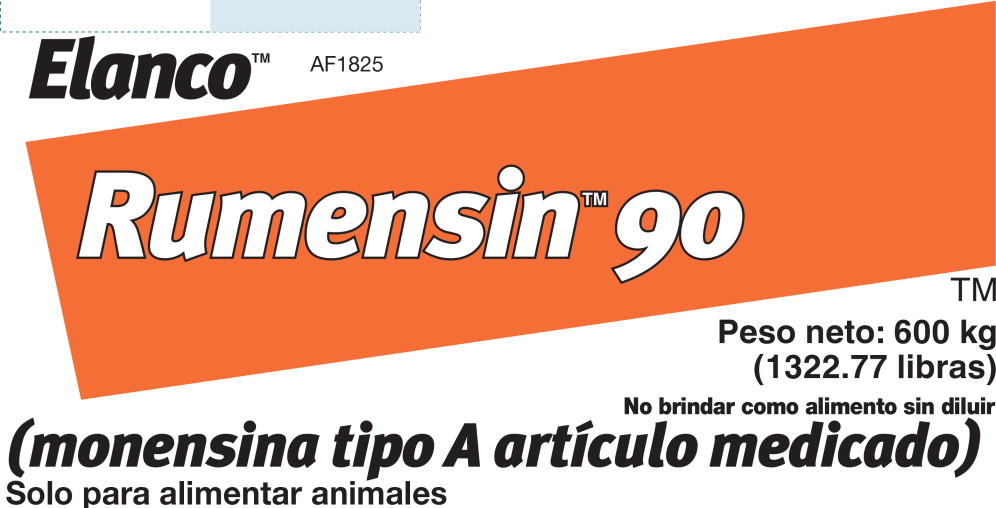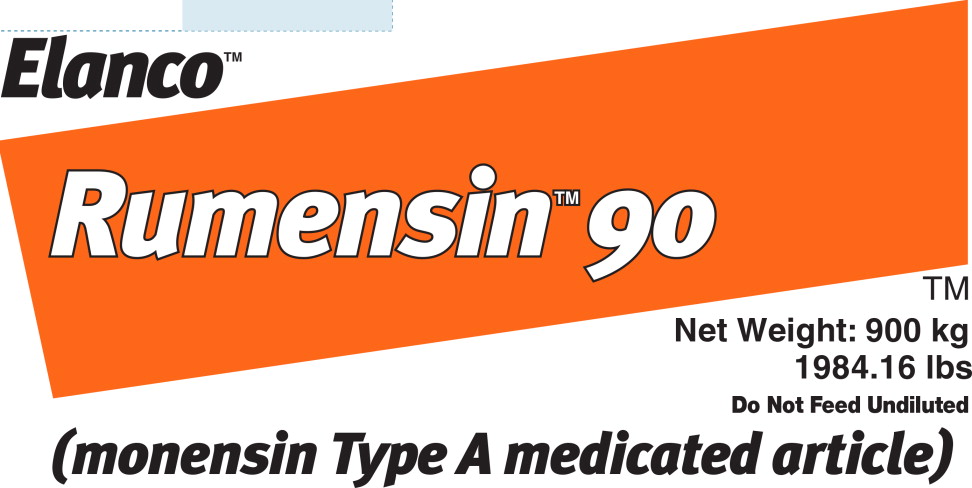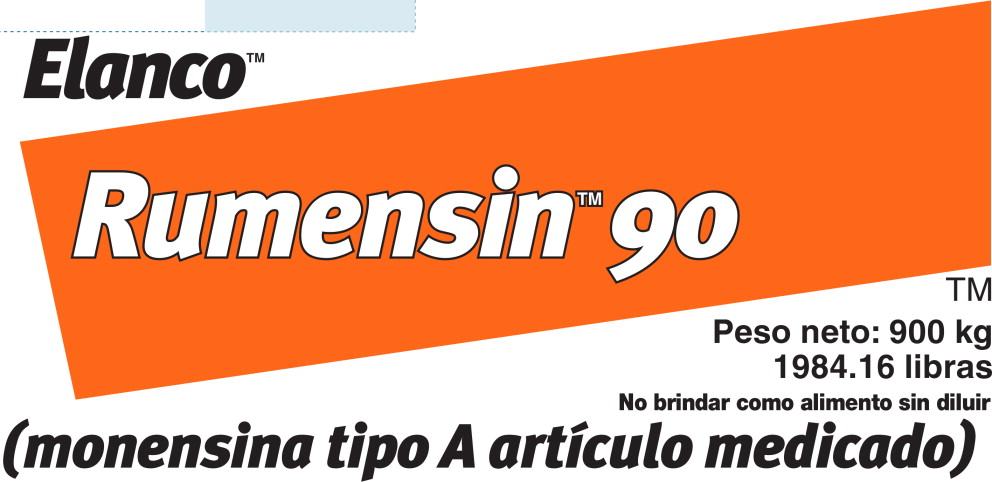 DRUG LABEL: Rumensin 90
NDC: 58198-1825 | Form: GRANULE
Manufacturer: Elanco US Inc.
Category: animal | Type: OTC TYPE A MEDICATED ARTICLE ANIMAL DRUG LABEL
Date: 20210804

ACTIVE INGREDIENTS: MONENSIN 200 g/1 kg

Elanco™

AF1825

Rumensin™ 90

Net Weight: 25 kg
(55.12 lbs)

Do Not Feed Undiluted

(monensin Type A
medicated article)

For Animal Feed Only

Growing beef steers and heifers fed in confinement for slaughter:

1. For improved feed efficiency.
2. For the prevention and control of coccidiosis due to Eimeria bovis and Eimeria zuernii.

Dairy Cows:

1. For increased milk production efficiency (production of marketable solids-corrected milk per unit of feed intake).

Growing beef steers and heifers on pasture (stocker, feeder, and slaughter) or in a dry lot:

1. For increased rate of weight gain.
2. For the prevention and control of coccidiosis due to Eimeria bovis and Eimeria zuernii.

Replacement beef and dairy heifers:

1. For increased rate of weight gain.
2. For the prevention and control of coccidiosis due to Eimeria bovis and Eimeria zuernii.

Beef Cows:

1. For improved feed efficiency when receiving supplemental feed.
2. For the prevention and control of coccidiosis due to Eimeria bovis and Eimeria zuernii.

Goats maintained in confinement except reproducing or lactating goats:

1. For the prevention of coccidiosis caused by Eimeria crandallis, Eimeria christenseni, and Eimeria ninakohlyakimovae.

Calves (excluding veal calves):

1. For the prevention and control of coccidiosis due to Eimeria bovis and Eimeria zuernii.

CAUTION: Do not allow horses or other equines access to feeds containing monensin. Ingestion of monensin by horses has been fatal. Monensin medicated cattle and goat feeds are safe for use in cattle and goats only. Consumption by unapproved species may result in toxic reactions. Feeding undiluted or mixing errors resulting in high concentrations of monensin has been fatal to cattle and could be fatal to goats. Must be thoroughly mixed in feeds before use. Do not exceed the levels of monensin recommended in the feeding directions as reduced average daily gains may result. Do not feed to lactating goats. If feed refusals containing monensin are fed to other groups of cattle, the concentration of monensin in the refusals and amount of refusals fed should be taken into consideration to prevent monensin overdosing.

YOU MAY NOTICE:

- Reduced voluntary feed intake in dairy cows fed monensin. This reduction increases with higher doses of monensin fed. Rule outmonensin as the cause of reduced feed intake before attributing to other causes such as illness, feed management, or the environment.
- Reduced milk fat percentage in dairy cows fed monensin. This reduction increases with higher doses of monensin fed.
- Increased incidence and treatment of cystic ovaries and metritis in dairy cows fed monensin.
- Reduced conception rates, increased services per animal, and extended days open and corresponding calving intervals in dairy cowsfed monensin.

Have a comprehensive and ongoing nutritional, reproductive and herd health program in place when feeding monensin to dairy cows.

NOT FOR HUMAN USE

WARNING:

A withdrawal time has not been established for pre-ruminating calves. Do not use in calves to be processed for veal. When mixing and handling Rumensin 90, use protective clothing, impervious gloves and a dust mask. Operators should wash thoroughly with soap and water after handling. If accidental eye contact occurs, immediately rinse with water.

To report adverse effects, access medical information, or obtain additional product information, call 1-800-428-4441.

Store at or below 25°C (77°F). Excursions permitted to 37°C (99°F). Not to be used after date printed on bag.

Restricted Drug (California) - Use Only as Directed

Approved by FDA under NADA # 095-735

Rumensin, Elanco and the diagonal bar logo are trademarks of Elanco or its affiliates. © 2021 Elanco or its affiliates.

Manufactured for: Elanco US, Inc., Greenfield, IN 46140, USA

Directions for use Read All Directions Carefully Before Mixing and Feeding

Active Drug Ingredients: Monensin USP, 90.7 g per pound.

1. Growing beef steers and heifers fed in confinement for slaughter:
  1. For improved feed efficiency. Feeding Directions: Thoroughly mix Rumensin 90 to make one ton of complete feed that provides 5 to 40 g/ton monensin on a 90% dry matter basis (Table 1). Feed complete feed (5 to 40 g/ton) continuously to growing beef steers and heifers in confinement to provide not less than 50 nor more than 480 mg monensin per head per day. No additional improvement in feed efficiency has been shown from feeding monensin at levels greater than 30 g/ton (360 mg monensin per head per day).
  2. For the prevention and control of coccidiosis due to Eimeria bovis and Eimeria zuernii.
    Feeding Directions: Feed continuously (10 to 40 g/ton) to provide 0.14 to 0.42 mg per pound of body weight per day, depending upon severity of challenge, up to a maximum of 480 mg of monensin per head per day.
2. Dairy Cows:
  1. For increased milk production efficiency (production of marketable solids-corrected milk per unit of feed intake).
    Feeding Directions:
    Total Mixed Rations (“complete feed”): Feed continuously to dry and lactating dairy cows a total mixed ration (“complete feed”) containing 11 to 22 g/ton monensin on a 100% dry matter basis (Table 2).
    Component Feeding Systems (including top dress): Feed continuously to dry and lactating dairy cows a Type C Medicated Feed containing 11 to 400 g/ton monensin (Table 3). The Type C Medicated Feed must be fed in a minimum of 1 pound of feed per cow per day to provide 185 to 660 mg/head/day monensin to lactating cows or 115 to 410 mg/head/day monensin to dry cows. This provides cows with similar amounts of monensin they would receive by consuming total mixed rations containing 11 to 22 g/ton monensin on a 100% dry matter basis.
    Directions for use continued on back of the bag
    Directions for use, continued
3. Growing beef steers and heifers on pasture (stocker, feeder, and slaughter) or in a dry lot: and
  Replacement beef and dairy heifers:
  1. For increased rate of weight gain. Feeding Directions: Feed at the rate of not less than 50 nor more than 200 mg per head per day in not less than one pound of Type C Medicated Feed; or after the 5th day, feed at the rate of 400 mg per head per day every other day in not less than 2 pounds of Type C Medicated Feed. The monensin concentration in the Type C Medicated Feed must be between 15 and 400 grams per ton. During the first 5 days, cattle should receive no more than 100 mg per day contained in not less than 1 pound of feed. Do not self feed.
  2. For the prevention and control of coccidiosis due to Eimeria bovis and Eimeria zuernii.
    Feeding Directions: Feed at a rate to provide 0.14 to 0.42 mg per pound body weight per day, depending upon severity of challenge, up to a maximum of 200 mg per head per day. The monensin concentration in Type C Medicated Feed must be between 15 and 400 grams per ton. During the first 5 days, cattle should receive no more than 100 mg per day contained in not less than 1 pound of feed.
  3. Type C free-choice medicated feeds.
    All Type C free-choice medicated feeds containing Rumensin must be manufactured according to an FDA-approved formula/specification. When using a formula/specification published in the Code of Federal Regulations (CFR), a Medicated Feed Mill license is not required. Use of Rumensin in a proprietary formula/specification not published in the CFR requires prior FDA approval and a Medicated Feed Mill license.
4. Beef Cows:
  1. For improved feed efficiency when receiving supplemental feed. Feeding Directions: Feed continuously at a rate of 50 to 200 mg per head per day. Blend into a minimum of 1 pound of Type C Medicated Feed and either hand feed or mix into the total ration. Feed (other than the Type C Medicated Feed containing Rumensin) can be restricted to 95% (of normal requirements) when 50 mg of monensin activity is fed, and to 90% at 200 mg. Cows on pasture or in dry lot must receive a minimum of 1 pound of Type C Medicated Feed per head per day. Additionally, a minimum of 16 pounds (air-dry basis) of roughage such as silage, haylage, ammoniated straw, hay or equivalent feedstuffs should be fed in order to meet NRC recommendations for beef cows to gain 0.25 to 0.75 pounds per head per day. Standing, dried winter range forage may not be of adequate quality to result in improved efficiency when supplemented with Rumensin. During the first 5 days, pastured cattle should receive no more than 100 mg per day contained in not less than 1 pound of feed. Do not self feed.
  2. For the prevention and control of coccidiosis due to Eimeria bovis and Eimeria zuernii.
    Feeding Directions: Feed at a rate of 0.14 to 0.42 mg per pound of body weight per day, depending upon severity of challenge, up to a maximum of 200 mg per head per day. During the first 5 days, pastured cattle should receive no more than 100 mg per day contained in not less than 1 pound of feed.
5. Goats maintained in confinement except reproducing or lactating goats:
  1. For prevention of coccidiosis caused by Eimeria crandallis, Eimeria christenseni and Eimeria ninakohlyakimovae.
    Feeding Directions: Feed complete feed (20 g/ton) continuously to goats as the sole ration (Table 1).
6. Calves (excluding veal calves):
  1. For the prevention and control of coccidiosis due to Eimeria bovis and Eimeria zuernii.
    Feed at a rate of 0.14 to 1.00 mg per pound of body weight per day, depending upon severity of challenge, up to a maximum of 200 mg of monensin per head per day. The monensin concentration in Type C Medicated Feed must be between 10 and 200 g/ton (Table 1).
7. Type B or C Medicated Feed Mixing Directions (Dry and Liquid):
  1. Dry or Liquid
    Thoroughly mix the following amounts of Rumensin 90 to make one ton of Type B or C Medicated Feed to provide the levels shown in Table 1.
    Dry Only - An Intermediate blending step should be performed to ensure an adequate mix.
  2. Liquid Limitations
    1. The supplement pH must be between 4.3 - 7.1.
    2. Stored liquid Type B Medicated Feeds containing Rumensin: For liquid feeds stored in recirculating tank systems:
      Recirculate immediately prior to use for not less than 10 minutes, moving not less than 1 percent of the tank contents per minute from the bottom of the tank to the top. Recirculate daily as described even when not used. • For liquid feeds stored in mechanical, air or other agitation-type tank systems: Agitate immediately prior to use for not less than 10 minutes creating a turbulence at the bottom of the tank that is visible at the top. Agitate daily as described even when not used.

CAUTION: Inadequate mixing (recirculation or agitation) of monensin Liquid Type B or C Medicated Feeds has resulted in increased monensin concentration which has been fatal to cattle and could be fatal to goats. • If feed refusals containing monensin are fed to other groups of cattle, the concentration of monensin in the refusals and amount of refusals fed should be taken into consideration to prevent monensin overdosing.

Directions for Use: Read All Directions Carefully Before Mixing and Feeding

Table 1: Mixing Directions for Cattle (excluding Dairy Cows), Goat and Calf Feeds
Desired Monensin Concentration in Medicated Feeda |  | Amount of Rumensin 90 Needed per ton
grams/ton | mg/lb feed | lbs. | grams
5 | 2.5 | 0.06 | 25.00
20 | 10 | 0.22 | 100.02
30 | 15 | 0.33 | 150.03
40 | 20 | 0.44 | 200.04
400 | 200 | 4.41 | 2000.40
1200 | 600 | 13.23 | 6001.19
a 90% dry matter basis

Table 2: Mixing Directions for Dairy Cow Total Mixed Rations (TMR)a
Amount of Rumensin 90 needed per ton of Type B, lbb | Desired monensin concentration in Type B Feed, g/ton; as-fed basisc | Dry matter of TMR, % |  | Desired monensin concentration, g/ton in TMRd
Amount of Rumensin 90 needed per ton of Type B, lbb | Desired monensin concentration in Type B Feed, g/ton; as-fed basisc | Dry matter of TMR, % | 11 |  | 15 | 22
 |  |  |  | lb of Type B (as-fed) needed per ton of TMR
5.51 | 500 | 50 | 22.00 |  | 30.00 | 44.00
5.51 | 500 | 60 | 26.40 |  | 36.00 | 52.80
15.88 | 1440 | 50 | 7.64 |  | 10.42 | 15.28
15.88 | 1440 | 60 | 9.17 |  | 12.50 | 18.33
88.20 | 8000 | 50 | 1.38 |  | 1.88 | 2.75
88.20 | 8000 | 60 | 1.65 |  | 2.25 | 3.30
a Amount of Type B (as-fed basis) needed to produce the TMR with desired level of monensin is as follows:
((Desired level of monensin in TMR g/ton) X (% dry matter of TMR)/g/ton of monensin in Type B) X 2000
Example Diet: Desire 11 g/ton monensin in TMR (dry matter basis), TMR contains 50% dry matter, & Type B contains 500 g/ton of monensin.
Example Solution: ((11 g/ton) X (0.50 dry matter of TMR) / 500 g/ton monensin in Type B) X 2000 = 22 lb of Type B needed per ton of TMR
b (Desired concentration of monensin in Type B feed, g/ton)/ 90.7 g/lb. Example: 500 g/ton / 90.7 g/lb = 5.51 lb Rumensin 90 per ton of Type B
c It is recommended that Type B feeds containing more than 1440 g/ton be further diluted before mixing into the TMR.
An example of further dilution would be a ratio of 1:10 of Type B Medicated Feed:Unmedicated Feed.
d100% dry matter basis

Table 3: Mixing Directions for Dairy Cows in Component Feeding Systems (Including Top Dress)a
Amount of Rumensin 90 needed per ton of Type B, lbb | Desired monensin concentration in Type B Feed, g/ton; as-fed basisc | Desired monensin concentration, g/ton in Component Feed
Amount of Rumensin 90 needed per ton of Type B, lbb | Desired monensin concentration in Type B Feed, g/ton; as-fed basisc | 50 |  | 200 |  | 400
 |  | lb of Type B (as-fed) needed per ton of component feed
5.51 | 500 | 200.00 |  | 800.00 |  | 1600.00
18.74 | 1700 | 58.82 |  | 235.29 |  | 470.59
44.10 | 4000 | 25.00 |  | 100.00 |  | 200.00
88.20 | 8000 | 12.50 |  | 50.00 |  | 100.00
a Amount of Type B (as-fed basis) needed to produce the component portion of the ration with desired level of monensin is as follows:
(Desired level of monensin in component, g/ton / g/ton of monensin in Type B) X 2000
Example Top Dress: Desire 50 g/ton monensin in component, & Type B contains 500 g/ton of monensin.
Example Solution: (50 g/ton / 500 g/ton monensin in Type B) X 2000 = 200 lb of Type B needed per ton of Top Dress
b (Desired concentration of monensin in Type B feed, g/ton)/ 90.7 g/lb.
Example: 500 g/ton / 90.7 g/lb = 5.51 lb Rumensin 90 per ton of Type B
c It is recommended that Type B feeds containing more than 1440 g/ton be further diluted before mixing into Top Dress.
An example of further dilution would be a ratio of 1:10 of Type B Medicated Feed: Unmedicated Feed.

BG103077A

PRINTED WITH
SOY INK

TAKE TIME

OBSERVE
LABEL DIRECTIONS

Elanco™

AF1825

Rumensin™ 90

Peso neto: 25 kg
(55.12 libras)

No brindar como alimento sin diluir

(monensina tipo A artículo medicado)

Solo para alimentar animales

Cría de novillos y vaquillonas alimentados en condiciones de encierro para faenar:

1. Para una mejor eficacia de la alimentación.
2. Para la prevención y el control de la coccidiosis a causa de Eimeria bovis y de Eimeria zuernii.

Vacas lecheras:

1. Para una mejor eficacia en la producción de leche (producción de leche corregida por sólidos comerciales por unidad de consumo de alimento).

Cría de novillos y vaquillonas con pastura (animal de cría, de engorde y para faena) o en un lote seco:

1. Para una mayor tasa de aumento de peso.
2. Para la prevención y el control de la coccidiosis a causa de Eimeria bovis y de Eimeria zuernii.

Reses de reemplazo y vacas lecheras:

1. Para una mayor tasa de aumento de peso.
2. Para la prevención de la coccidiosis a causa de Eimeria bovis y de Eimeria zuernii.

Vacas para consumo:

1. Para una mejor eficacia de la alimentación al recibir suplementos.
2. Para la prevención y el control de la coccidiosis a causa de Eimeria bovis y de Eimeria zuernii.

Cabras que estén encerradas, excepto las cabras lactantes o para reproducción:

1. Para la prevención de la coccidiosis a causa de Eimeria crandallis, Eimeria christenseni y Eimeria ninakohlyakimovae

Terneros (sin incluir los que se sacrifican para carnear):

1. Para la prevención y el control de la coccidiosis a causa de Eimeria bovis y de Eimeria zuernii.

PRECAUCIÓN: No permita que caballos u otros equinos accedan al agua que contiene monensina. La ingesta de monensina en caballos ha sido mortal. Los alimentos medicados con monensina para ganado y para cabras es seguro para el uso en ganado y cabras solamente. El consumo en especies no aprobadas puede provocar reacciones tóxicas. Errores de mezcla o de falta de dilución en el alimento que derivan en concentraciones elevadas de monensina han sido mortales para el ganado y podrían serlo también para las cabras. Debe mezclarse bien con los alimentos antes de usar. No superar los niveles de monensina que se recomiendan en las instrucciones de alimentación, ya que pueden producirse menores aumentos diarios promedio. No brindar como alimento a las cabras lactantes. Si los alimentos rechazados con monensina se ofrecen a otros grupos de ganado, la concentración de monensina en dichos alimentos y la cantidad de estos deben tenerse en cuenta a fin de evitar sobredosis de monensina.

PUEDE NOTARSE LO SIGUIENTE:

- Menor ingesta voluntaria de alimentos en las vacas lecheras alimentadas con monensina. Esta reducción aumenta al incrementar ladosis de monensina. Descartar que la monensina haya sido la causa de la menor ingesta de alimentos antes de atribuirla a otras causas, como enfermedades, control de los alimentos o el medioambiente.
- Menor porcentaje graso en la leche de las vacas lecheras alimentadas con monensina. Esta reducción aumenta al incrementar la dosisde monensina.
- Mayor incidencia y tratamiento de los ovarios quísticos y de la metritis en las vacas lecheras que reciben monensina.
- Menores tasas de concepción, aumento de los servicios por animal y prolongación de los días fértiles y de los correspondientes intervalos de parto en las vacas lecheras que reciben monensina.

Se implementa un programa sanitario nutricional, reproductivo y ganadero integral y continuo al alimentar a las vacas lecheras con monensina.

NO USAR EN SERES HUMANOS

ADVERTENCIA:

No se determinó un tiempo de retiro para los terneros prerrumiantes. No usar en terneros que se procesarán para carnear. Al mezclar y al manipular Rumensin 90, usar ropa protectora, guantes impermeables y una máscara antipolvo. Los operadores deben lavarse bien con agua y jabón luego de manipular el producto. Si se produce contacto accidental con los ojos, enjuague inmediatamente con agua.

Para informar sobre efectos adversos, acceder a información médica u obtener más información sobre el producto, llame al 1-800-428-4441.

Almacenar a una temperatura igual o inferior a 25 °C (77 °F). Se permiten desviaciones de hasta 37 °C (99 °F).

No debe usarse después de la fecha impresa en la bolsa.

Fármaco restringido (California). Usar únicamente según las instrucciones.

Aprobado por la FDA bajo NADA # 095-735.

Rumensin, Elanco y el logo de la barra diagonal son marcas de Elanco o sus afiliadas. © 2021 Elanco or its affiliates.

Elanco US, Inc., Greenfield, IN 46140 EE. UU.

Instrucciones de uso Lea atentamente todas las instrucciones antes de mezclar y ofrecer como alimento

Principios farmacológicos activos: Monensina USP; 90.7 g por libra.

1. Cría de novillos y vaquillonas alimentados en condiciones de encierro para faenar:
  1. Para una mejor eficacia de la alimentación. Instrucciones de alimentación: Mezclar bien Rumensin 90 hasta formar una tonelada de alimento completo que brinde de 5 a 40 g/tonelada de monensina sobre una base de materia seca al 90 % (Tabla 1). Ofrecer el alimento completo (de 5 a 40 g/tonelada) en forma continua a las crías de novillos y vaquillonas hasta proporcionar no menos de 50 ni más de 480 mg de monensina por cabeza por día. No se demostró otra mejora en la eficacia de la alimentación por ofrecer monensina en los alimentos en niveles superiores a los 30 g/tonelada (360 mg de monensina por cabeza por día).
  2. Para la prevención y el control de la coccidiosis a causa de Eimeria bovis y de Eimeria zuernii.
    Instrucciones de alimentación: Alimentar en forma continua (de 10 a 40 g/tonelada) hasta brindar de 0.14 a 0.42 mg por libra de peso corporal por día, según la gravedad del caso, hasta un máximo de 480 mg de monensina por cabeza por día.
2. Vacas lecheras:
  1. Para una mejor eficacia en la producción de leche (producción de leche corregida por sólidos comerciales por unidad de consumo de alimento).
    Instrucciones de alimentación:
    Total de raciones mezcladas (“alimentación completa”): Ofrecer como alimento en forma continua a vacas lecheras lactantes y secas una ración mezclada total (“alimentación completa”) con 11 a 22 g/toneladas de monensina sobre una base de materia seca del 100 % (Tabla 2). Sistemas de alimentación en componentes (incluso agregados): Ofrecer como alimento en forma continua a vacas lecheras lactantes y secas un alimento medicado de tipo C con 11 a 400 g/tonelada de monensina (Tabla 3). El alimento medicado de tipo C debe ofrecerse en un mínimo de 1 libra de alimento por vaca por día hasta brindar de 185 a 660 mg/cabeza/día de monensina a vacas lactantes o de 115 a 410 mg/cabeza/día de monensina a vacas secas. Esto brinda a las vacas cantidades de monensina similares a las que recibirían si consumieran un total de raciones mezcladas con de 11 a 22 g/toneladas de monensina sobre una base de materia seca del 100 %.
    Las instrucciones de uso continúan en la parte de atrás de la bolsa
    Instrucciones de uso, continuación
3. Cría de novillos y vaquillonas con pastura (animal de cría, de engorde y para faena) o en un lote seco; y
  Reses de reemplazo y vacas lecheras:
  1. Para una mayor tasa de aumento de peso. Instrucciones de alimentación: Alimentar a una tasa de no menos de 50 ni de más de 200 mg por cabeza por día en no menos de una libra de alimento medicado de tipo C, o, después del 5.° día, alimentar día por media a una tasa de 400 mg por cabeza por día con no menos de 2 libras de alimento medicado de tipo C. La concentración de monensina en el alimento medicado de tipo C debe ser de entre 15 y 400 gramos por tonelada. Durante los primeros 5 días, el ganado debe recibir no más de 100 mg por día en no menos de 1 libra de alimento. No ofrecer para autoalimentación.
  2. Para la prevención y el control de la coccidiosis a causa de Eimeria bovis y de Eimeria zuernii.
    Instrucciones de alimentación: Alimentar a una tasa de 0.14 a 0.42 mg por libra de peso corporal por día, según la gravedad del caso, hasta un máximo de 200 mg por cabeza por día. La concentración de monensina en el alimento medicado de tipo C debe ser de entre 15 y 400 gramos por tonelada. Durante los primeros 5 días, el ganado debe recibir no más de 100 mg por día en no menos de 1 libra de alimento.
  3. Piensos medicamentosos de elección libre de tipo C. Todos los piensos medicamentosos de elección libre de tipo C que contengan Rumensin deben fabricarse según una especificación/fórmula aprobada por la FDA. Si se usa una especificación/fórmula publicada en el Código de Reglamentos Federales (Code of Federal Regulations, CFR), no es necesaria una licencia de molienda para piensos medicamentosos. El uso de Rumensin en una especificación/fórmula patentada no publicada en el CFR exige aprobación previa por parte de la FDA y una licencia de molienda para piensos medicamentosos.
4. Vacas para consumo:
  1. Para una mejor eficacia de la alimentación al recibir suplementos. Instrucciones de alimentación: Alimentar en forma continua a una tasa de 50 a 200 mg por cabeza por día. Mezclar con un mínimo de 1 libra de alimento medicado de tipo C, y ofrecer con la mano o mezclar con la ración total. La alimentación (excepto los alimentos medicados de tipo C que contengan Rumensin) puede limitarse al 95 % (de los requisitos normales) al alimentar con 50 mg de actividad de monensina y al 90 % con 200 mg. Las vacas con pastura o en lote seco deben recibir un mínimo de 1 libra de alimento medicado de tipo C por cabeza por día. Asimismo, debe ofrecerse un mínimo de 16 libras (base seca de aire) de forraje, como ensilaje, henolaje, paja con amonio, heno o piensos equivalentes, para poder cumplir con las recomendaciones del Consejo de Investigación Nacional (National Research Council, NRC) para vacas para carne maduras respecto de aumentar de 0.25 a 0.75 libras por cabeza por día. Puede que la búsqueda de comida de pie en zonas invernadas secas no tenga la calidad adecuada para mejorar la eficacia al brindarse con suplementos de Rumensin. Durante los primeros 5 días, el ganado con pastura debe recibir no más de 100 mg por día en no menos de 1 libra de alimento. No ofrecer para autoalimentación.
  2. Para la prevención y el control de la coccidiosis a causa de Eimeria bovis y de Eimeria zuernii.
    Instrucciones de alimentación: Alimentar a una tasa de 0.14 a 0.42 mg por libra de peso corporal por día, según la gravedad del caso, hasta un máximo de 200 mg por cabeza por día. Durante los primeros 5 días, el ganado con pastura debe recibir no más de 100 mg por día en no menos de 1 libra de alimento.
5. Cabras que estén encerradas, excepto las cabras lactantes o para reproducción:
  1. Para la prevención de la coccidiosis a causa de Eimeria crandallis, Eimeria christenseni y Eimeria ninakohlyakimovae.
    Instrucciones de alimentación: Brindar el alimento completo (20 g/tonelada) en forma continua a las cabras como única ración (Tabla 1).
6. Terneros (sin incluir los que se sacrifican para carnear):
  1. Para la prevención y el control de la coccidiosis a causa de Eimeria bovis y de Eimeria zuernii.
    Alimentar a una tasa de 0.14 a 1.00 mg por libra de peso corporal por día, según la gravedad del caso, hasta un máximo de 200 mg de monensina por cabeza por día. La concentración de monensina en el alimento medicado de tipo C debe ser de entre 10 y 200 g/tonelada (Tabla 1).
7. Instrucciones para mezclar alimento medicado de tipo B o de tipo C (seco y líquido):
  1. Seco o líquido
    Mezclar bien las siguientes cantidades de Rumensin 90 hasta formar una tonelada de alimento medicado de tipo B o de tipo C y hasta alcanzar los niveles que se muestran en la Tabla 1. Seco solamente: Debe realizarse un paso intermedio de mezcla para garantizar una mezcla adecuada.
  2. Limitaciones líquidas
    1. El pH del suplemento debe ser de 4.3-7.1.
    2. Alimentos medicados de tipo B líquidos almacenados con Rumensin: Para alimentos líquidos almacenados en sistemas de tanques de recirculación: Recircular inmediatamente antes de usar durante no menos de 10 minutos, y trasladar no menos de 1 % del contenido del tanque por minuto desde el fondo hasta la parte superior del tanque. Recircular a diario como se describe, aun cuando no se usa.
      - Para alimentos líquidos almacenados en sistemas de tanques mecánicos, aéreos o con otro tipo de agitación: Agitar inmediatamente antes de usar durante no menos de 10 minutos hasta generar una turbulencia en el fondo del tanque que sea visible en la parte superior. Agitar a diario como se describe, aun cuando no se usa.

PRECAUCIÓN:

La mezcla inadecuada (recirculación o agitación) de alimentos medicados de tipo B o de tipo C líquidos con monensina produjo un aumento de la concentración de monensina que fue mortal para el ganado y que podría serlo también para las cabras. • Si los alimentos rechazados con monensina se ofrecen a otros grupos de ganado, la concentración de monensina en dichos alimentos y la cantidad de estos deben tenerse en cuenta a fin de evitar sobredosis de monensina.

Instrucciones de uso: Lea atentamente todas las instrucciones antes de mezclar y ofrecer como alimento

Tabla 1: Instrucciones de mezcla para alimentos de ganado (sin incluir las vacas lecheras), cabras y terneros
Concentración deseada de monensina en alimentos medicadosa |  | Cantidad de Rumensin 90 necesaria por tonelada
gramos/tonelada | mg/libra de alimento | libras | gramos
5 | 2.5 | 0.06 | 25.00
20 | 10 | 0.22 | 100.02
30 | 15 | 0.33 | 150.03
40 | 20 | 0.44 | 200.04
400 | 200 | 4.41 | 2000.40
1200 | 600 | 13.23 | 6001.19
a base de materia seca del 90 %

Tabla 2: Instrucciones de mezcla para raciones combinadas totales (total mixed rations, TMR) en vacas lecherasa
Cantidad de Rumensin 90 necesaria por tonelada de tipo B, librab | Concentración deseada de monensina en alimento de tipo B, g/tonelada; base alimentariac | Materia seca de las TMR,% | Concentración deseada de monensina, g/tonelada en TMRd
Cantidad de Rumensin 90 necesaria por tonelada de tipo B, librab | Concentración deseada de monensina en alimento de tipo B, g/tonelada; base alimentariac | Materia seca de las TMR,% | 11 | 15 | 22
 |  |  | libra de tipo B (base alimentaria) necesaria por tonelada de TMR
5.51 | 500 | 50 60 | 22.00 26.40 | 30.00 36.00 | 44.00 52.80
15.88 | 1440 | 50 60 | 7.64 9.17 | 10.42 12.50 | 15.28 18.33
88.20 | 8000 | 50 60 | 1.38 1.65 | 1.88 2.25 | 2.75 3.30
aLa cantidad de tipo B (base alimentaria) necesaria para producir TMR con un nivel deseado de monensina es la siguiente:
((Nivel deseado de monensina en TMR g/tonelada) X (% materia seca de TMR)/g/tonelada de monensina en tipo B) X 2000
Ejemplo de dieta: Deseada de 11 g/tonelada de monensina en TMR (base de materia seca); las TMR contienen 50 % de materia seca, y el tipo B contiene 500 g/tonelada de monensina.
Ejemplo de solución: ((11 g/tonelada) X (0.50 materia seca de TMR)/500 g/tonelada de monensina en el tipo B) X 2000 = 22 libras de tipo B necesarias por tonelada de TMR
b(Concentración deseada de monensina en alimento de tipo B, g/tonelada)/90.7 g/libra.
Ejemplo: 500 g/tonelada /90.7 g/libra = 5.51 libra Rumensin 90 por tonelada de tipo B
cSe recomienda que los alimentos de tipo B que contengan más de 1440 g/tonelada continúen diluyéndose antes de mezclar con las TMR. Un ejemplo de dilución adicional sería una proporción de 1:10 de alimento medicado de tipo B: Alimento no medicado.
dbase de materia seca del 100 %

Tabla 3: Instrucciones de mezcla para vacas lecheras en sistemas de alimentación por componente (incluso agregados)a
Cantidad de Rumensin 90 necesaria por tonelada de tipo B, librab | Concentración deseada de monensina en alimento de tipo B, g/tonelada; base alimentariac | Concentración deseada de monensina, g/tonelada en alimentación por componente
Cantidad de Rumensin 90 necesaria por tonelada de tipo B, librab | Concentración deseada de monensina en alimento de tipo B, g/tonelada; base alimentariac | 50 |  | 200 |  | 400
 |  | libra de tipo B (base alimentaria) necesaria por tonelada de alimentación por componente
5.51 | 500 | 200.00 |  | 800.00 |  | 1600.00
18.74 | 1700 | 58.82 |  | 235.29 |  | 470.59
44.10 | 4000 | 25.00 |  | 100.00 |  | 200.00
88.20 | 8000 | 12.50 |  | 50.00 |  | 100.00
a La cantidad de tipo B (base alimentaria) necesaria para producir la porción por componente de la ración con un nivel deseado de monensina es la siguiente: (Nivel deseado de monensina en componente, g/tonelada/g/tonelada de monensina en tipo B) X 2000
Ejemplo de agregado: Ideal de 50 g/tonelada de monensina en el componente, y el tipo B contiene 500 g/tonelada de monensina.
Ejemplo de solución: (50 g/tonelada/500 g/tonelada de monensina en el tipo B) X 2000 = 200 libras de tipo B necesarias por tonelada de agregado
b (Concentración deseada de monensina en alimento de tipo B, g/tonelada)/90.7 g/libra.
Ejemplo: 500 g/tonelada/90.7 g/libra = 5.51 libra Rumensin 90 por tonelada de tipo B
c Se recomienda que los alimentos de tipo B que contengan más de 1440 g/tonelada continúen diluyéndose antes de mezclar con el agregado.
Un ejemplo de dilución adicional sería una proporción de 1:10 de alimento medicado de tipo B: Alimento no medicado.

BG103077B

PRINTED WITH
SOY INK

TÓMESE SU TIEMPO

SIGA LAS INSTRUCCIONES DEL
PROSPECTO

Principal Display Panel 25 kg Bag Label

Elanco ™

AF1825

Rumensin ™ 90

Net Weight: 25 kg

(55.12 lbs)

Do Not Feed Undiluted

(monensin Type A
medicated article)

Principal Display Panel 25 kg Bag Label

Elanco ™

AF1825

Rumensin ™ 90

Peso neto: 25 kg

(55.12 libras)

No brindar como alimento sin diluir

(monensina tipo A
articulo medicado)

Principal Display Panel 600 kg Bag Label

Elanco ™

AF1825

Rumensin ™ 90

Net Weight: 600 kg

(1322.77 lbs)

Do Not Feed Undiluted

(monensin Type A medicated article)

Principal Display Panel 600 kg Bag Label

Elanco ™

AF1825

Rumensin ™ 90

Peso neto: 600 kg

(1322.77 libras)

No brindar como alimento sin diluir

(monensina tipo A articulo medicado)

Principal Display Panel 900 kg Bag Label

Elanco ™

Rumensin ™ 90

Net Weight: 900 kg

1984.16 lbs

Do Not Feed Undiluted

(monensin Type A medicated article)

Principal Display Panel 900 kg Bag Label

Elanco ™

Rumensin ™ 90

Peso neto: 900 kg

1984.16 libras

No brindar como alimento sin diluir

(monensina tipo A articulo medicado)